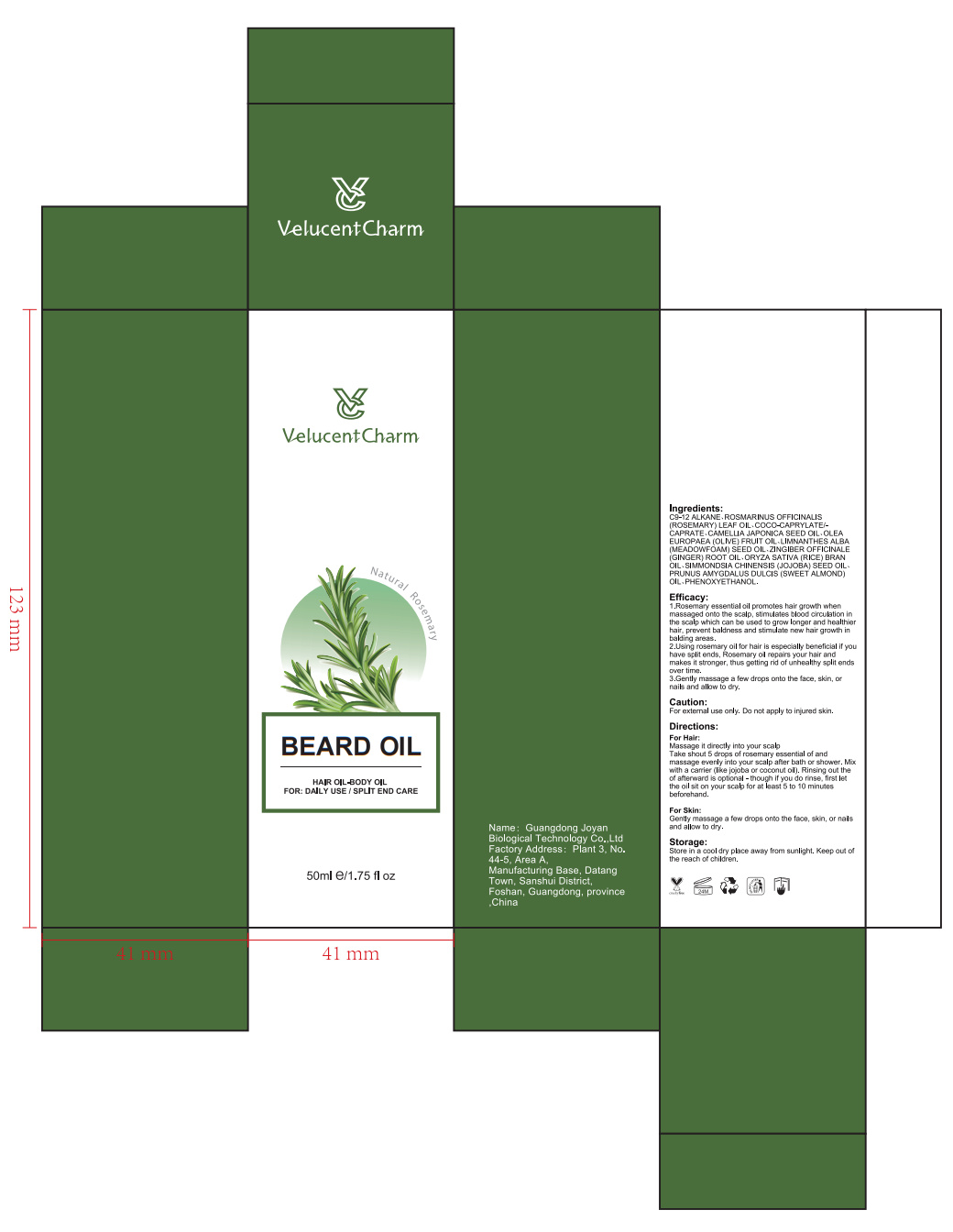 DRUG LABEL: Velucent Charm
NDC: 84716-110 | Form: OIL
Manufacturer: Shenzhen Boyang E-commerce Co.
Category: otc | Type: HUMAN OTC DRUG LABEL
Date: 20240927

ACTIVE INGREDIENTS: METHYLPROPANEDIOL 2.4875 g/50 g; ERYTHRITOL 0.75 g/50 g; GLYCERIN 10 g/50 g
INACTIVE INGREDIENTS: WATER 35.593 g/50 g

ACTIVE INGREDIENTS

GLYCERIN 20%
METHYLPROPANEDIOL 4.975%
ERYTHRITOL 1.5%
HYDROGENATED STARCH HYDROLYSATE 0.4%
1,2-HEXANEDIOL 0.39%

PURPOSE

1.Rosemary essential oil promotes hair growth whenmassaqed onto the scalp,stimulates blood circulation inthe scalp which can be used to grow longer and healthie!hair,prevent baldness and stimulate new hair growth inbalding areas.

2.Using rosemary oil for hair is especially beneficial if youhave split ends,Rosemary oil repairs your hair andmakes it stronger, thus getting rid of unhealthy split endsover time.

3.Gently massage a few drops onto the face, skin, ornails and allow to dry.

Uses

For Hair:Massage it directly into your scalpTake shout 5 drops of rosemary essential of andmassage evenly into your scalp after bath or shower. ixwith a carrier (like jojoba or coconut oil). Rinsing out theof afterward is optional -thouah if you do rinse, first letthe oil sit on your scalp for at least 5 to 10 minutesbeforehand.
For Skin:Gently massage a few drops onto the face, skin, or nailsand allow to dry.

Warnings

Please place it out of the reach of infants; lt is recommended to have a skin test (inside the wrist or behind the ear) before use.lf you feel uncomfortable,please stop using it.

Stop use and ask a doctor if

lt is recommended to have a skin test (inside the wrist orbehind the ear) before use.If you feel uncomfortable,please stop using it.

Do not use

on damaged or broken skin.

Keep out of reach of children

Please place it out of the reach of infants；If swallowed, get medical help or contact a Poison Control Center right away.

When using this product

FOR EXTERNAL USE ONIY.

keep out of eyes. Rinse with water to remove.

uses and storage method

Caution:

For external use only, Do not apply to injured skin.

Directions:

For Hair:

Massage it directly into your scalpTake shout 5 drops of rosemary essential of andmassage evenly into your scalp after bath or shower. ixwith a carrier (like jojoba or coconut oil). Rinsing out theof afterward is optional -thouah if you do rinse, first letthe oil sit on your scalp for at least 5 to 10 minutesbeforehand.
For Skin:

Gently massage a few drops onto the face, skin, or nailsand allow to dry.

Storage:

Store in a cool dry place away from sunlight. Keep out ofthe reach of children.

INACTIVE INGREDIENT SECTON

PHENOXYETHANOL,CARBOMER,TRIETHANOLAMINE,PEG-40 HYDROGENATED CASTOR OIL,CAPRYLHYDROXAMIC ACID,

CITRIC ACID,CI 19140